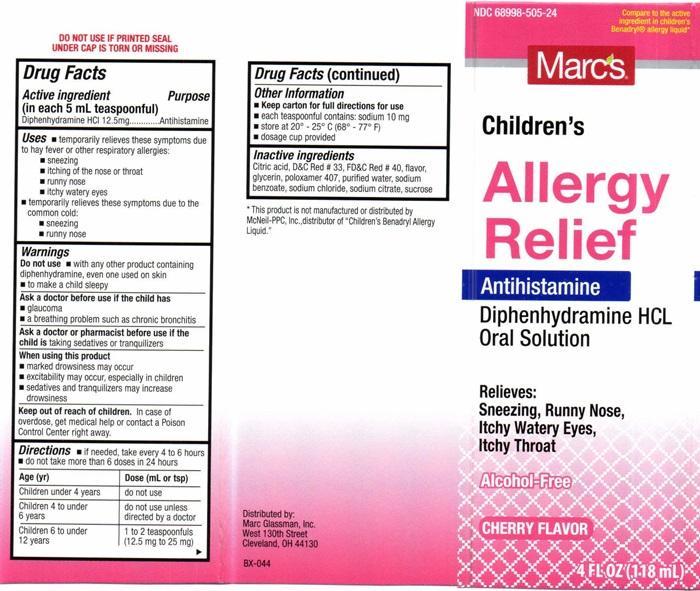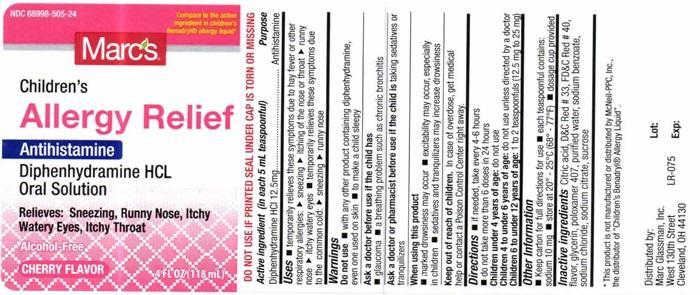 DRUG LABEL: Childrens Allergy Relief
NDC: 68998-505 | Form: LIQUID
Manufacturer: Marc Glassman, Inc.
Category: otc | Type: HUMAN OTC DRUG LABEL
Date: 20251219

ACTIVE INGREDIENTS: DIPHENHYDRAMINE HYDROCHLORIDE 12.5 mg/5 mL
INACTIVE INGREDIENTS: ANHYDROUS CITRIC ACID; D&C RED NO. 33; FD&C RED NO. 40; GLYCERIN; POLOXAMER 407; WATER; SODIUM BENZOATE; SODIUM CHLORIDE; SODIUM CITRATE; SUCROSE

Drug Facts Active ingredient

Active ingredient

(in each 5 mL teaspoonful)

Diphenhydramine HCL 12.5 mg

Purpose

Antihistamine

Keep out of reach of children. In case of overdose, get medical help or contact a Poison Control Center right away.

Uses

- temporarily relives these symptoms due to hay fever or other respiratory allergies:
- sneezing
- itching of the nose or throat
- runny nose
- itchy watery eyes
- temporarily relieves these symptoms due to the common cold:
- sneezing
- runny nose

Warnings

Do not use• With any other product containing diphenhydramine, even one used on skin

- to make a child sleepy

Ask a doctor before use if the child has

- glaucoma
- a breathing problem such as chronic bronchitis

Ask a doctor or pharmacist before use if the child is

taking sedatives or tranquilizers

When using this product

- marked drowsiness may occur
- excitability may occur, especially in childrren
- sedatives and tranquilizers may increase drowsiness

Directions

- if needed, take every 4 to 6 hours
- do not take more than 6 doses in 24 hours

Age (yr) | Dose (mL or tsp)
Children under 4 years | do not use
Children 4 to under 6 years | do not use unless directed by a doctor
Children 6 to under 12 years | 1 to 2 teaspoonfuls (12.5 mg to 25 mg)

Other Information

- Keep carton for full directions for use
- each teaspoonful contains: sodium 10 mg
- store at 20° - 25° C (68° - 77° F)
- dosage cup provided

Inactive ingredients

Citric acid, D and C Red # 33 FD and C Red # 40, flavor, glycerin, poloxamer 407, purified water, sodium benzoate, sodium chloride, sodium citrate, sucrose

Marcs Childrens Allergy Relief Product Label

NDC 68998-505-24

Compare to the active ingredient in children's Benadryl® allergy liquid*

Marcs

Children's

Allergy

Relief

Antihistamine

Diphenhydramine HCL

Oral Solution

Relieves:

Sneezing, Runny Nose,

Itchy Watery Eyes,

Itchy Throat

Alcohol-Free

CHERRY FLVOR

4 FL OZ (118 mL)

DO NOT USE IF PRINTED SEAL UNDER CAP IS TORN OR MISSING

* This product is not manufactured or distributed by McNeil-PPC, Inc., distributor of "Children's Benadryl Allergy Liquid."

Distributed By:

Marc Glassman, Inc.

West 130th Street

Cleveland, OH 44130

BX-044

Internal Label - LR-075 Lot: Exp:

res